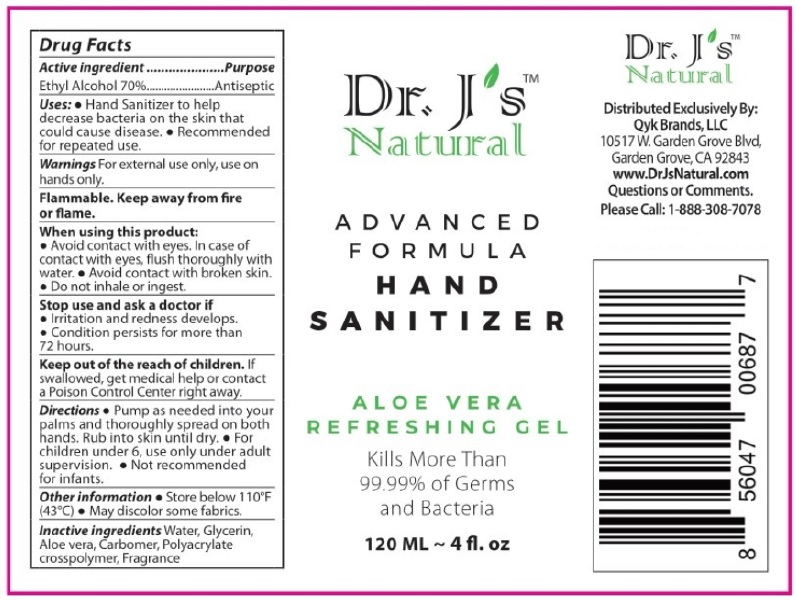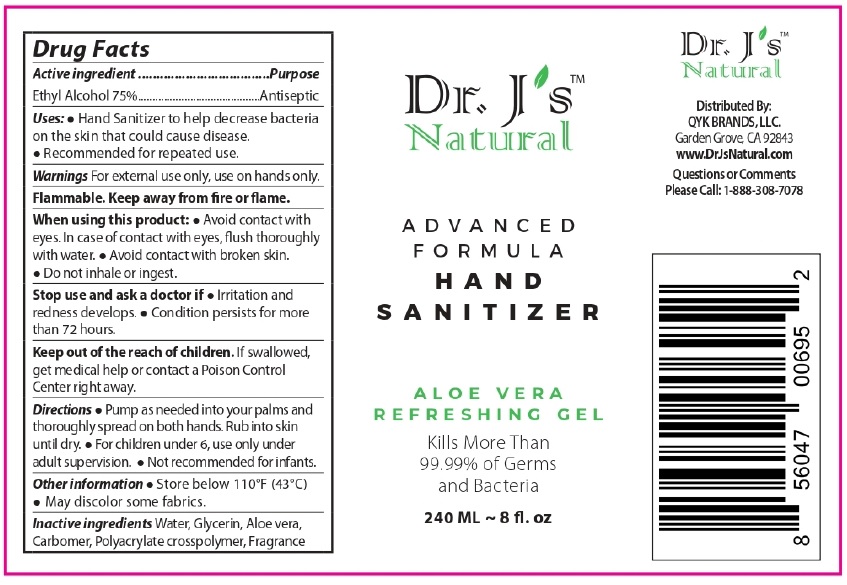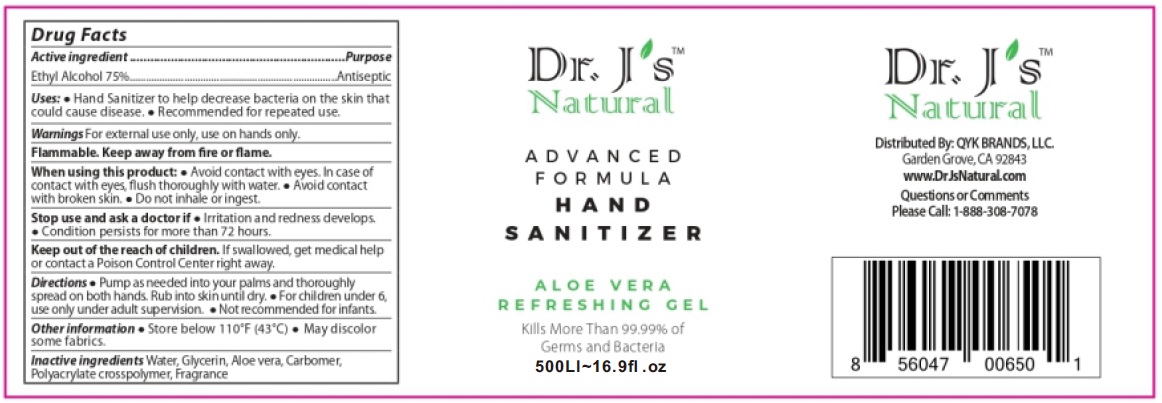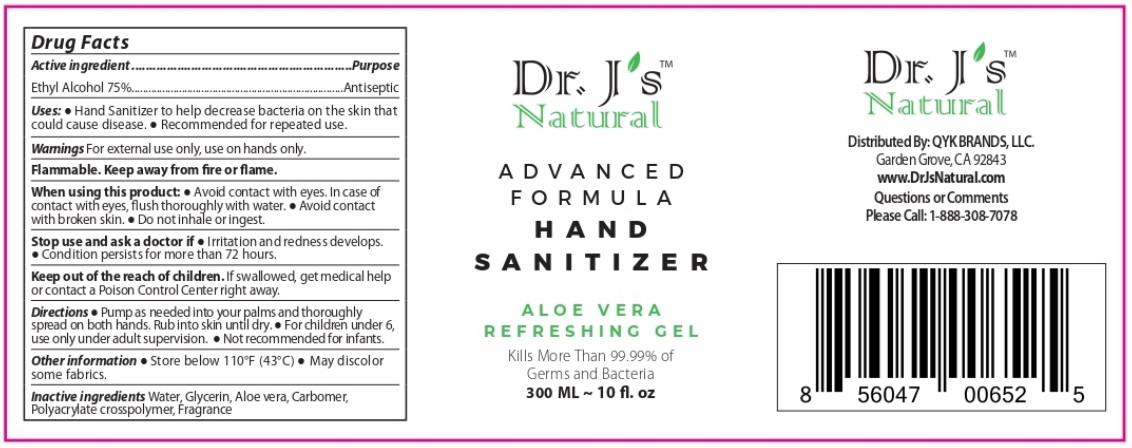 DRUG LABEL: QYK Brands
NDC: 74416-171 | Form: GEL
Manufacturer: Guangzhou C-kang Biotechnology Co., Ltd.
Category: otc | Type: HUMAN OTC DRUG LABEL
Date: 20200701

ACTIVE INGREDIENTS: ALCOHOL 75 mL/100 mL
INACTIVE INGREDIENTS: WATER; GLYCERIN; ALOE VERA LEAF; CARBOMER HOMOPOLYMER, UNSPECIFIED TYPE; AMMONIUM ACRYLOYL DIMETHYLTAURATE/METHACRYLATE, DIMETHYLACRYLAMIDE AND METHACRYLIC ACID COPOLYMER, PPG-3 GLYCERYL TRIACRYLATE CROSSLINKED (100000 MW)

Dr. J's™ Natural ADVANCED FORMULA HAND SANITIZER

Active Ingredient

Ethyl Alcohol 75%

Purpose

Antiseptic

INDICATIONS AND USAGE

Uses: • Hand Sanitizer to help decrease bacteria on the skin that could cause disease. • Recommended for repeated use.

WARNINGS

Warnings For external use only, use on hands only.

Flammable. Keep away from fire or flame.

When using this product: • Avoid contact with eyes. In case of contact with eyes, flush thoroughly with water. • Avoid contact with broken skin. • Do not inhale or ingest.

Stop use and ask doctor if • Irritation and redness develops. • Condition persists for more than 72 hours.

KEEP OUT OF REACH OF CHILDREN

Keep out of the reach for children. If swallowed, get medical help or contact a Poison Control Center right away.

DOSAGE AND ADMINISTRATION

Directions • Pump as needed into your palms and thoroughly spread on both hands. Rub into skin until dry. • For children under 6, use only under adult supervision. • Not recommended for infants.

Other information • Store below 110°F (43°C) • May discolor some fabrics.

INACTIVE INGREDIENT

Inactive ingredients Water, Glycerin, Aloe vera, Carbomer, Polyacrylate crosspolymer, Fragrance

ALOE VERA REFRESHING GEL

Kills More Than 99.99% of Germs and Bacteria

Distributed By:

QYK BRANDS, LLC.

Garden Grove, CA 92843

www.DrJsNatural.com

Questions or Comments

Please Call: 1-888-308-7078